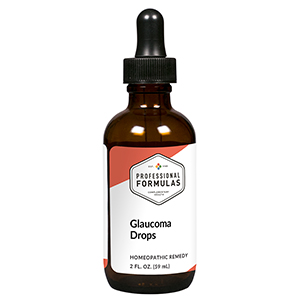 DRUG LABEL: Glaucoma Drops
NDC: 63083-2074 | Form: LIQUID
Manufacturer: Professional Complementary Health Formulas
Category: homeopathic | Type: HUMAN OTC DRUG LABEL
Date: 20190815

ACTIVE INGREDIENTS: PLECTRANTHUS BARBATUS ROOT OIL 2 [hp_X]/59 mL; BILBERRY 2 [hp_X]/59 mL; EUPHRASIA STRICTA 3 [hp_X]/59 mL; GELSEMIUM SEMPERVIRENS ROOT 3 [hp_X]/59 mL; SPIGELIA ANTHELMIA WHOLE 3 [hp_X]/59 mL; GOLDENSEAL 5 [hp_X]/59 mL; ACONITUM NAPELLUS WHOLE 6 [hp_X]/59 mL; AMARYLLIS BELLADONNA WHOLE 6 [hp_X]/59 mL; BOS TAURUS EYE 6 [hp_X]/59 mL; BRYONIA ALBA ROOT 12 [hp_X]/59 mL; PHOSPHORUS 12 [hp_X]/59 mL
INACTIVE INGREDIENTS: ALCOHOL; WATER

C74

ACTIVE INGREDIENTS

Coleus forskohlii 2X
Vaccinium myrtillus 2X
Euphrasia officinalis 3X
Gelsemium sempervirens 3X
Spigelia anthelmia 3X, 6X
Hydrastis canadensis 5X
Aconitum napellus 6X
Belladonna 6X
Eye 6X, 12X, 30X
Bryonia 12X
Phosphorus 12X

QUESTIONS

Professional Formulas

PO Box 2034 Lake Oswego, OR 97035

INDICATIONS

For the temporary relief of occasional eye pain, blurred vision, or distorted vision.*

PURPOSE

*Claims based on traditional homeopathic practice, not accepted medical evidence. Not FDA evaluated.

WARNINGS

Severe or persistent symptoms may be a sign of a serious condition. Consult a doctor promptly if symptoms are accompanied by severe eye pain with nausea, or sudden vision disturbance or loss. Keep out of the reach of children. In case of overdose, get medical help or contact a poison control center right away. If pregnant or breastfeeding, ask a healthcare professional before use.

Keep out of the reach of children.

PREGNANCY OR BREAST FEEDING

If pregnant or breastfeeding, ask a healthcare professional before use.

DIRECTIONS

Place drops under tongue 30 minutes before/after meals. Adults and children 12 years and over: Take 10 drops up to 3 times per day. Consult a physician for use in children under 12 years of age.

OTHER INFORMATION

Tamper resistant. If seal is broken, do not use. After opening, close container tightly and store at room temperature away from heat.

INACTIVE INGREDIENTS

20% ethanol, purified water.

LABEL

Est 1985

Professional Formulas

Complementary Health

Glaucoma Drops

Homeopathic Remedy

2 FL. OZ. (59 mL)